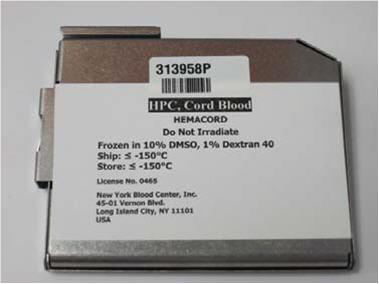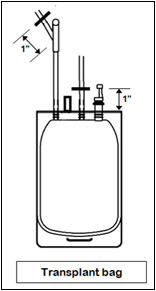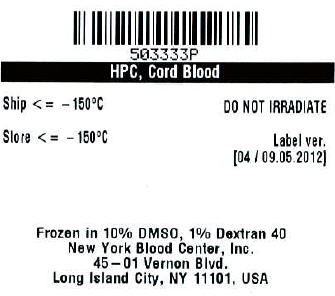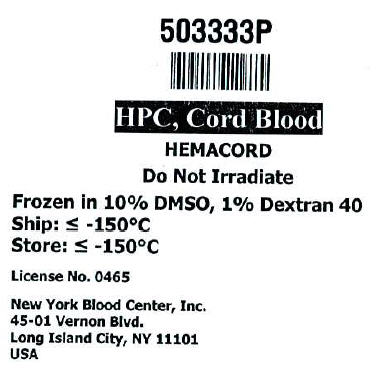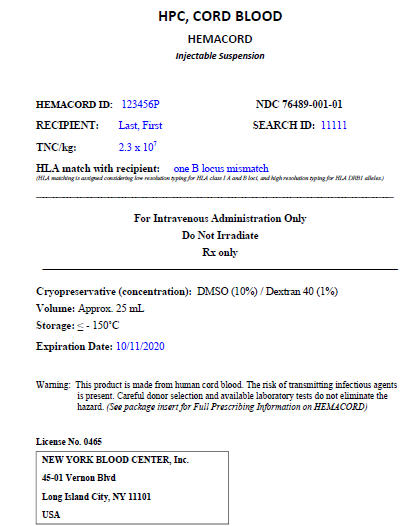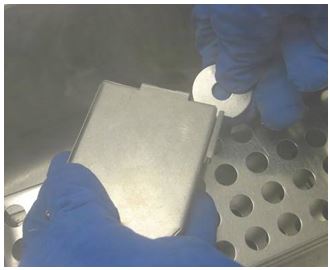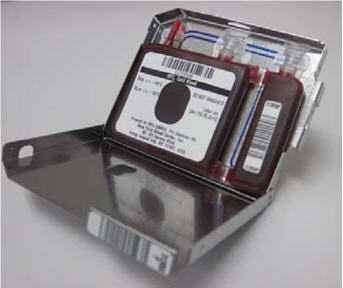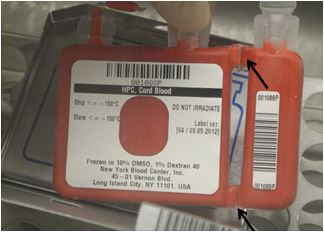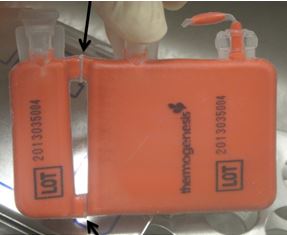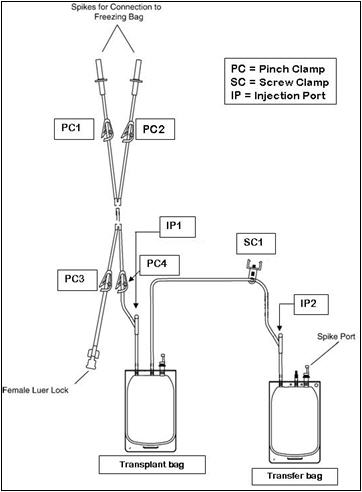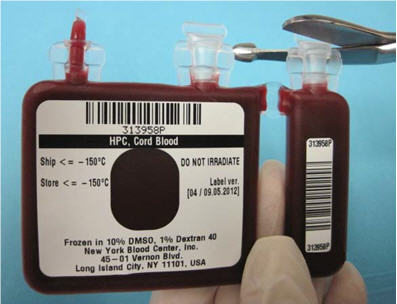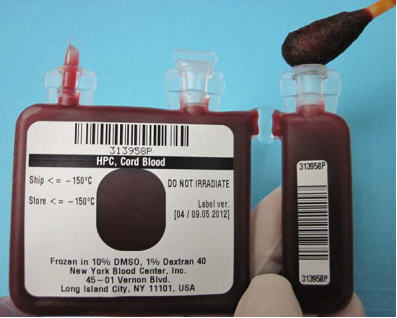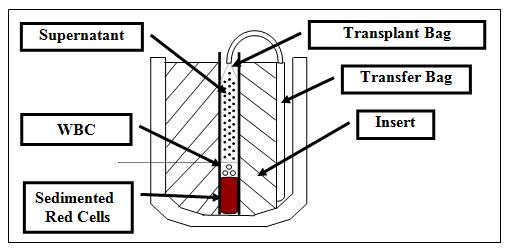 DRUG LABEL: HemaCord
NDC: 76489-001 | Form: INJECTION
Manufacturer: New York Blood Center
Category: other | Type: CELLULAR THERAPY
Date: 20221019

ACTIVE INGREDIENTS: HUMAN CORD BLOOD HEMATOPOIETIC PROGENITOR CELL 500000000 1/25 mL
INACTIVE INGREDIENTS: DIMETHYL SULFOXIDE

HIGHLIGHTS OF PRESCRIBING INFORMATION

These highlights do not include all the information needed to use HEMACORD safely and effectively. See full prescribing information for HEMACORD.
HEMACORD (HPC, Cord Blood)
Injectable Suspension for Intravenous Use
Initial U.S. Approval: 2011

WARNING: FATAL INFUSION REACTIONS, GRAFT VERSUS HOST DISEASE, ENGRAFTMENT SYNDROME AND GRAFT FAILURE

WARNING: FATAL INFUSION REACTIONS, GRAFT VERSUS
HOST DISEASE, ENGRAFTMENT SYNDROME, AND GRAFT
FAILURE
See full prescribing information for complete boxed warning.

- Fatal infusion reactions: Monitor patients during infusion and discontinue for severe reactions. (5.1, 5.2)
- Graft-vs-host disease (GVHD): GVHD may be fatal. Administration of immunosuppressive therapy may decrease the risk of GVHD (5.3)
- Engraftment syndrome: Engraftment syndrome may be fatal. Treat engraftment syndrome promptly with corticosteroids (5.4)
- Graft failure: Graft failure may be fatal. Monitor patients for laboratory evidence of hematopoietic recovery (5.5)

RECENT MAJOR CHANGES

Boxed Warning 5/2015

Contraindications (4.0) 5/2015

1 INDICATIONS AND USAGE

HEMACORD HPC, Cord Blood, is an allogeneic cord blood hematopoietic progenitor cell therapy indicated for use in unrelated donor hematopoietic progenitor cell transplantation procedures in conjunction with an appropriate preparative regimen for hematopoietic and immunologic reconstitution in patients with disorders affecting the hematopoietic system that are inherited, acquired, or result from myeloablative treatment (1)
The risk benefit assessment for an individual patient depends on the patient characteristics, including disease, stage, risk factors, and specific manifestations of the disease, on characteristics of the graft, and on other available treatments or types of hematopoietic progenitor cells (1)

2 DOSAGE AND ADMINISTRATION

- For intravenous use only
- Do not irradiate
- Unit selection and administration of HEMACORD should be done under the direction of a physician experienced in hematopoietic progenitor cell transplantation (2)
- The recommended minimum dose is 2.5 X 10^7 nucleated cells/kg at cryopreservation (2.1)
- Do not administer HEMACORD through the same tubing with other products except for normal saline (2.3)

3 DOSAGE FORMS AND STRENGTHS

Each unit contains a minimum of 5 x 10^8 total nucleated cells with at least 1.25 x 10^6 viable CD34+ cells at the time of cryopreservation. The exact pre-cryopreservation nucleated cell content of each unit is provided on the container label and accompanying records

4 CONTRAINDICATIONS

None

5 WARNINGS AND PRECAUTIONS

- Hypersensitivity Reactions (5.1)
- Infusion Reactions (5.2)
- Graft-versus-Host Disease (5.3)
- Engraftment Syndrome (5.4)
- Graft Failure (5.5)
- Malignancies of Donor Origin (5.6)
- Transmission of Serious Infections (5.7)
- Transmission of Rare Genetic Diseases (5.8)

6 ADVERSE REACTIONS

Mortality, from all causes, at 100 days post-transplant was 25% (5, 6.1)
The most common infusion-related adverse reactions (≥5%) are hypertension, vomiting, nausea, bradycardia, and fever (6.1)

To report SUSPECTED ADVERSE REACTIONS, contact the New York Blood Center at 1-866-767-NCBP (1-866-767-6227) and FDA at 1-800-FDA-1088 or www.fda.gov/medwatch

8 USE IN SPECIFIC POPULATIONS

Pregnancy: No animal or human data. Use only if clearly needed (8.1)

FULL PRESCRIBING INFORMATION

WARNING: FATAL INFUSION REACTIONS, GRAFT VERSUS HOST DISEASE, ENGRAFTMENT SYNDROME AND GRAFT FAILURE

Fatal infusion reactions: HEMACORD administration can result in serious, including fatal, infusion reactions. Monitor patients and discontinue HEMACORD infusion for severe reactions. [See Warnings and Precautions (5.1, 5.2)]
Graft-vs-host disease (GVHD): GVHD is expected after administration of HEMACORD, and may be fatal. Administration of immunosuppressive therapy may decrease the risk of GVHD. [See Warnings and Precautions (5.3)]
Engraftment syndrome: Engraftment syndrome may progress to multiorgan failure and death. Treat engraftment syndrome promptly with corticosteroids. [See Warnings and Precautions (5.4)]
Graft failure: Graft failure may be fatal. Monitor patients for laboratory evidence of hematopoietic recovery. Prior to choosing a specific unit of HEMACORD, consider testing for HLA antibodies to identify patients who are alloimmunized. [See Warnings and Precautions (5.5)]

1 INDICATIONS AND USAGE

HEMACORD, HPC (Hematopoietic Progenitor Cell), Cord Blood, is an allogeneic cord blood hematopoietic progenitor cell therapy indicated for use in unrelated donor hematopoietic progenitor stem cell transplantation procedures in conjunction with an appropriate preparative regimen for hematopoietic and immunologic reconstitution in patients with disorders affecting the hematopoietic system that are inherited, acquired, or result from myeloablative treatment.

The risk benefit assessment for an individual patient depends on the patient characteristics, including disease, stage, risk factors, and specific manifestations of the disease, on characteristics of the graft, and on other available treatments or types of hematopoietic progenitor cells.

2 DOSAGE AND ADMINISTRATION

- For intravenous use only.
- Do not irradiate.

Unit selection and administration of HEMACORD should be done under the direction of a physician experienced in hematopoietic progenitor cell transplantation.

2.1 Dosing

The recommended minimum dose is 2.5 x 10^7 nucleated cells/kg at cryopreservation. Multiple units may be required in order to achieve the appropriate dose.

Matching for at least 4 of 6 HLA-A antigens, HLA-B antigens, and HLA-DRB1 alleles is recommended. The HLA typing and nucleated cell content for each individual unit of HEMACORD are documented on the container label and/or in accompanying records.

2.2 Preparation for Infusion

HEMACORD should be prepared by a trained healthcare professional.

- Do not irradiate HEMACORD.
- See the appended detailed instructions for preparation of HEMACORD for infusion.
- Once prepared for infusion, HEMACORD may be stored at 4 to 25°C for up to 4 hours if DMSO is not removed, and at 4°C for up to 24 hours if DMSO is removed in a washing procedure [see Instructions for Preparation for Infusion] .
- The recommended limit on DMSO administration is 1 gram per kg body weight per day [see Warnings and Precautions (5.2) and Overdosage (10)].

2.3 Administration

HEMACORD should be administered under the supervision of a qualified healthcare professional experienced in hematopoietic progenitor cell transplantation.

1. Confirm the identity of the patient for the specified unit of HEMACORD prior to administration.
2. Confirm that emergency medications are available for use in the immediate area.
3. Ensure the patient is hydrated adequately.
4. Premedicate the patient 30 to 60 minutes before the administration of HEMACORD. Premedication can include any or all of the following: antipyretics, histamine antagonists, and corticosteroids.
5. Inspect the product for any abnormalities such as unusual particulates and for breaches of container integrity prior to administration. Prior to infusion, discuss all such product irregularities with the laboratory issuing the product for infusion.
6. Administer HEMACORD by intravenous infusion. Do not administer in the same tubing concurrently with products other than 0.9% Sodium Chloride, Injection (USP). HEMACORD may be filtered through a 170 to 260 micron filter designed to remove clots. Do NOT use a filter designed to remove leukocytes.
7. For adults, begin infusion of HEMACORD at 100 milliliters per hour and increase the rate as tolerated. For children, begin infusion of HEMACORD at 1 milliliter per kg per hour and increase as tolerated. The infusion rate should be reduced if the fluid load is not tolerated. The infusion should be discontinued in the event of an allergic reaction or if the patient develops a moderate to severe infusion reaction. [See Warnings and Precautions (5.2) and Adverse Reactions (6).]
8. Monitor the patient for adverse reactions during, and for at least six hours after, administration. Because HEMACORD contains lysed red cells that may cause renal failure, careful monitoring of urine output is also recommended.

3 DOSAGE FORMS AND STRENGTHS

Each unit of HEMACORD contains a minimum of 5.0 x 10^8 total nucleated cells with a minimum of 1.25 x 10^6 viable CD34+ cells, suspended in 10% dimethyl sulfoxide (DMSO) and 1% Dextran 40, at the time of cryopreservation.

The exact pre-cryopreservation nucleated cell content is provided on the container label and in accompanying records.

4 CONTRAINDICATIONS

None

5 WARNINGS AND PRECAUTIONS

5.1 Hypersensitivity Reactions

Allergic reactions may occur with infusion of HPC, Cord Blood, including HEMACORD. Reactions include bronchospasm, wheezing, angioedema, pruritus and hives [see Adverse Reactions (6)] . Serious hypersensitivity reactions, including anaphylaxis, also have been reported. These reactions may be due to dimethyl sulfoxide (DMSO), Dextran 40, or a plasma component of HEMACORD.

HEMACORD may contain residual antibiotics if the cord blood donor was exposed to antibiotics in utero. Patients with a history of allergic reactions to antibiotics should be monitored for allergic reactions following HEMACORD administration.

5.2 Infusion Reactions

Infusion reactions are expected to occur and include nausea, vomiting, fever, rigors or chills, flushing, dyspnea, hypoxemia, chest tightness, hypertension, tachycardia, bradycardia, dysgeusia, hematuria, and mild headache. Premedication with antipyretics, histamine antagonists, and corticosteroids may reduce the incidence and intensity of infusion reactions.

Severe reactions, including respiratory distress, severe bronchospasm, severe bradycardia with heart block or other arrhythmias, cardiac arrest, hypotension, hemolysis, elevated liver enzymes, renal compromise, encephalopathy, loss of consciousness, and seizure also may occur. Many of these reactions are related to the amount of DMSO administered. Minimizing the amount of DMSO administered may reduce the risk of such reactions, although idiosyncratic responses may occur even at DMSO doses thought to be tolerated. The actual amount of DMSO depends on the method of preparation of the product for infusion. Limiting the amount of DMSO infused to no more than 1 gram per kilogram per day is recommended [see Overdosage (10)].

If infusing more than one unit of HPC, Cord Blood, on the same day, do not administer subsequent units until all signs and symptoms of infusion reactions from the prior unit have resolved.

Infusion reactions may begin within minutes of the start of infusion of HEMACORD, although symptoms may continue to intensify and not peak for several hours after completion of the infusion. Monitor the patient closely during this period. When a reaction occurs, discontinue the infusion and institute supportive care as needed.

5.3 Graft-versus-Host Disease

Acute and chronic graft-versus-host disease (GVHD) may occur in patients who have received HEMACORD. Classic acute GVHD is manifested as fever, rash, elevated bilirubin and liver enzymes, and diarrhea. Patients transplanted with HEMACORD also should receive immunosuppressive drugs to decrease the risk of GVHD. [See Adverse Reactions (6.1).]

5.4 Engraftment Syndrome

Engraftment syndrome is manifested as unexplained fever and rash in the peri-engraftment period. Patients with engraftment syndrome also may have unexplained weight gain, hypoxemia, and pulmonary infiltrates in the absence of fluid overload or cardiac disease. If untreated, engraftment syndrome may progress to multiorgan failure and death. Begin treatment with corticosteroids once engraftment syndrome is recognized in order to ameliorate the symptoms. [See Adverse Reactions (6.1).]

5.5 Graft Failure

Primary graft failure, which may be fatal, is defined as failure to achieve an absolute neutrophil count greater than 500 per microliter blood by Day 42 after transplantation. Immunologic rejection is the primary cause of graft failure. Patients should be monitored for laboratory evidence of hematopoietic recovery. Consider testing for HLA antibodies in order to identify patients who are alloimmunized prior to transplantation and to assist with choosing a unit with a suitable HLA type for the individual patient. [See Adverse Reactions (6.1).]

5.6 Malignancies of Donor Origin

Patients who have undergone HPC, Cord Blood, transplantation may develop post-transplant lymphoproliferative disorder (PTLD), manifested as a lymphoma-like disease favoring non-nodal sites. PTLD is usually fatal if not treated.

The incidence of PTLD appears to be higher in patients who have received antithymocyte globulin. The etiology is thought to be donor lymphoid cells transformed by Epstein-Barr virus (EBV). Serial monitoring of blood for EBV DNA may be warranted in high-risk groups.

Leukemia of donor origin also has been reported in HPC, Cord Blood, recipients. The natural history is presumed to be the same as that for de novo leukemia.

5.7 Transmission of Serious Infections

Transmission of infectious disease may occur because HEMACORD is derived from human blood. Disease may be caused by known or unknown infectious agents. Donors are screened for increased risk of infection with human immunodeficiency virus (HIV), human T-cell lymphotropic virus (HTLV), hepatitis B virus (HBV), hepatitis C virus (HCV), T. pallidum, T. cruzi, West Nile Virus (WNV), transmissible spongiform encephalopathy (TSE) agents, and vaccinia. Donors are also screened for clinical evidence of sepsis, and communicable disease risks associated with xenotransplantation. Maternal blood samples are tested for HIV types 1 and 2, HTLV types I and II, HBV, HCV, T. pallidum, WNV, and T. cruzi. HEMACORD is tested for sterility. There may be an effect on the reliability of the sterility test results if the cord blood donor was exposed to antibiotics in utero. These measures do not totally eliminate the risk of transmitting these or other transmissible infectious diseases and disease agents. Report the occurrence of a transmitted infection to the New York Blood Center at 1-866-767-NCBP (1-866-767-6227).

Testing is also performed for evidence of donor infection due to cytomegalovirus (CMV). Test results may be found on the container label and/or in accompanying records.

5.8 Transmission of Rare Genetic Diseases

HEMACORD may transmit rare genetic diseases involving the hematopoietic system for which donor screening and/or testing has not been performed [see Adverse Reactions (6.1)] . Cord blood donors have been screened by family history to exclude inherited disorders of the blood and marrow. HEMACORD has been tested to exclude donors with sickle cell anemia, and anemias due to abnormalities in hemoglobins C, D, and E. Because of the age of the donor at the time HEMACORD collection takes place, the ability to exclude rare genetic diseases is severely limited.

6 ADVERSE REACTIONS

Day-100 mortality from all causes was 25%.

The most common infusion-related adverse reactions (≥ 5%) are hypertension, vomiting, nausea, bradycardia, and fever.

6.1 Clinical Trials Experience

Because clinical trials are conducted under widely varying conditions, adverse reaction rates observed in the clinical trials of a drug cannot be directly compared to rates in the clinical trials of another drug and may not reflect the rates observed in practice.

Infusion Reactions

The data described in Table 1 reflect exposure to 442 infusions of HPC, Cord Blood, (from multiple cord blood banks) in patients treated using a total nucleated cell dose ≥2.5 x 10^7/kg on a single-arm trial or expanded access use (The COBLT Study). The population was 60% male and the median age was 5 years (range 0.05-68 years), and included patients treated for hematologic malignancies, inherited metabolic disorders, primary immunodeficiencies, and bone marrow failure. Preparative regimens and graft-vs.-host disease prophylaxis were not standardized. The most common infusion reactions were hypertension, vomiting, nausea, and sinus bradycardia. Hypertension and any grades 3-4 infusion related reactions occurred more frequently in patients receiving HPC, Cord Blood, in volumes greater than 150 milliliters and in pediatric patients. The rate of serious adverse cardiopulmonary reactions was 0.8%.

Table 1: Incidence of Infusion-Related Adverse Reactions Occurring in ≥ 1% of Infusions (The COBLT Study)
 | Any grade | Grade 3-4
Any reaction | 65.4% | 27.6%
Hypertension | 48.0% | 21.3%
Vomiting | 14.5% | 0.2%
Nausea | 12.7% | 5.7%
Sinus bradycardia | 10.4% | 0
Fever | 5.2% | 0.2%
Sinus tachycardia | 4.5% | 0.2%
Allergy | 3.4% | 0.2%
Hypotension | 2.5% | 0
Hemoglobinuria | 2.1% | 0
Hypoxia | 2.0% | 2.0%

Information on infusion reactions was available from voluntary reports for 244 patients who received HEMACORD. The population included 56% males and 44% females with median age of 25 years (range 0.2-73 years). Preparative regimens and graft-vs.-host disease prophylaxis were not standardized. The reactions were not graded. An infusion reaction occurred in 18% of patients. The most common infusion reactions, occurring in ≥ 1% of patients, were hypertension (14%), nausea (5%), vomiting (4%), hypoxemia (3%), dyspnea (1%), tachycardia (1%), and cough (1%). The rate of serious adverse cardiopulmonary reactions was 0.1%.

Other Adverse Reactions

For other adverse reactions, the raw clinical data from the docket were pooled for 1299 (120 adult and 1179 pediatric) patients transplanted with HPC, Cord Blood, (from multiple cord blood banks) with total nucleated cell dose ≥ 2.5 x 10^7/kg. Of these, 66% (n=862) underwent transplantation as treatment for hematologic malignancy. The preparative regimens and graft-vs.-host disease prophylaxis varied. The median total nucleated cell dose was 6.4 x 10^7/kg (range, 2.5-73.8 x 10^7/kg). For these patients, Day-100 mortality from all causes was 25%. Primary graft failure occurred in 16%; 42% developed grades 2-4 acute graft-vs.-host disease; and 19% developed grades 3-4 acute graft-vs.-host disease.

Data from published literature and from observational registries, institutional databases, and cord blood bank reviews reported to the docket for HPC, Cord Blood, (from multiple cord blood banks) revealed nine cases of donor cell leukemia, one case of transmission of infection, and one report of transplantation from a donor with an inheritable genetic disorder. The data are not sufficient to support reliable estimates of the incidences of these events.

In a study of 364 patients, 15% of the patients developed engraftment syndrome.

8 USE IN SPECIFIC POPULATIONS

8.1 Pregnancy

Pregnancy Category C. Animal reproduction studies have not been conducted with HEMACORD. It is also not known whether HEMACORD can cause fetal harm when administered to a pregnant woman or can affect reproduction capacity. There are no adequate and well-controlled studies in pregnant women. HEMACORD should be used during pregnancy only if the potential benefit justifies the potential risk to the fetus.

8.4 Pediatric Use

HPC, Cord Blood, has been used in pediatric patients with disorders affecting the hematopoietic system that are inherited, acquired, or resulted from myeloablative treatment. [See Dosage and Administration (2), Adverse Reactions (6), and Clinical Studies (14).]

8.5 Geriatric Use

Clinical studies of HPC, Cord Blood, (from multiple cord blood banks) did not include sufficient numbers of subjects aged 65 years and over to determine whether they respond differently than younger subjects. In general, administration of HEMACORD to patients over age 65 years should be cautious, reflecting their greater frequency of decreased hepatic, renal, or cardiac function, and of concomitant disease or other drug therapy.

8.6 Renal Disease

HEMACORD contains Dextran 40 which is eliminated by the kidneys. The safety of HEMACORD has not been established in patients with renal insufficiency or renal failure.

10 OVERDOSAGE

10.1 Human Overdosage Experience

There has been no experience with overdosage of HPC, Cord Blood, in human clinical trials. Single doses of HEMACORD up to 57.6 x 10^7 TNC/kg have been administered. HPC, Cord Blood, prepared for infusion may contain dimethyl sulfoxide (DMSO). The maximum tolerated dose of DMSO has not been established, but it is customary not to exceed a DMSO dose of 1 gm/kg/day when given intravenously. Several cases of altered mental status and coma have been reported with higher doses of DMSO.

10.2 Management of Overdose

For DMSO overdosage, general supportive care is indicated. The role of other interventions to treat DMSO overdosage has not been established.

11 DESCRIPTION

HEMACORD consists of hematopoietic progenitor cells, monocytes, lymphocytes, and granulocytes from human cord blood for intravenous infusion. Blood recovered from umbilical cord and placenta is volume reduced and partially depleted of red blood cells and plasma.

The active ingredient is hematopoietic progenitor cells which express the cell surface marker CD34. The potency of cord blood is determined by measuring the numbers of total nucleated cells (TNC) and CD34+ cells, and cell viability. Each unit of HEMACORD contains a minimum of 5 x 10^8 total nucleated cells with at least 1.25 x 10^6 viable CD34+ cells at the time of cryopreservation. The cellular composition of HEMACORD depends on the composition of cells in the blood recovered from the umbilical cord and placenta of the donor. The actual nucleated cell count, the CD34^+ cell count, the ABO group, and the HLA typing are listed on the container label and/or accompanying records sent with each individual unit.

HEMACORD has the following inactive ingredients: dimethyl sulfoxide (DMSO), Dextran 40, and citrate phosphate dextrose adenine 1 (CPDA-1). When prepared for infusion according to instructions, the infusate contains the following inactive ingredients: Dextran 40, human serum albumin, and residual DMSO and citrate phosphate dextrose adenine 1 (CPDA-1).

12. CLINICAL PHARMACOLOGY

12.1 Mechanism of Action

Hematopoietic stem/progenitor cells from HPC, Cord Blood, migrate to the bone marrow where they divide and mature. The mature cells are released into the bloodstream, where some circulate and others migrate to tissue sites, partially or fully restoring blood counts and function, including immune function, of blood-borne cells of marrow origin. [See Clinical Studies (14).]

In patients with enzymatic abnormalities due to certain severe types of storage disorders, mature leukocytes resulting from HPC, Cord Blood, transplantation may synthesize enzymes that may be able to circulate and improve cellular functions of some native tissues. However, the precise mechanism of action is unknown.

14 CLINICAL STUDIES

The effectiveness of HPC, Cord Blood, as defined by hematopoietic reconstitution, was demonstrated in one single-arm prospective study, and in retrospective reviews of data from an observational database for HEMACORD and data in the dockets and public information. Of the 1299 patients in the docket and public data, 66% (n=862) underwent transplantation as treatment for hematologic malignancy. Results for patients who received a total nucleated cell dose ≥2.5 x 10^7/kg are shown in Table 2. Neutrophil recovery is defined as the time from transplantation to an absolute neutrophil count more than 500 per microliter. Platelet recovery is the time to a platelet count more than 20,000 per microliter. Erythrocyte recovery is the time to a reticulocyte count greater than 30,000 per microliter. The total nucleated cell dose and degree of HLA match were inversely associated with the time to neutrophil recovery in the docket data.

Table 2: Hematopoietic Recovery for Patients Transplanted with HPC, Cord Blood, Total Nucleated Cell (TNC) Dose ≥ 2.5 x 10^7/kg
Data Source | The COBLT Study* | Docket* and Public Data* | HEMACORD
Design | Single-arm prospective | Retrospective | Retrospective
Number of patients | 324 | 1299 | 155
Median age (years) (range) | 4.6 (0.07 – 52.2) | 7.0 (<1 – 65.7) | 14.5 (0.2 – 72.6)
Gender | 59% male 41% female | 57% male 43% female | 54% male 46% female
Median TNC Dose (x 10^7/kg) (range) | 6.7 (2.6 – 38.8) | 6.4 (2.5 – 73.8) | 4.9 (2.5 – 39.8)
Neutrophil Recovery at Day 42 (95% CI) | 76% (71% – 81%) | 77% (75% – 79%) | 83% (76% – 88%)
Platelet Recovery at Day 100 of 20,000/microliter (95% CI) | 57% (51% – 63%) | - | 77% (69% – 84%)
Platelet Recovery at Day 100 of 50,000/microliter (95% CI) | 46% (39% – 51%) | 45% (42% – 48%) | -
Erythrocyte Recovery at Day 100 (95% CI) | 65% (58% – 71%) | - | -
Median time to Neutrophil Recovery | 27 days | 25 days | 20 days
Median time to Platelet Recovery of 20,000/microliter | 90 days | - | 45 days
Median time to Platelet Recovery of 50,000/microliter | 113 days | 122 days | -
Median time to Erythrocyte Recovery | 64 days | - | -
*HPC, Cord Blood (from multiple cord blood banks)

16 HOW SUPPLIED/STORAGE AND HANDLING

HEMACORD is supplied as a cryopreserved cell suspension in a sealed bag containing a minimum of 5 x 10^8 total nucleated cells with a minimum of 1.25 x 10^6 viable CD34+ cells in a volume of 25 milliliters (NDC# 76489-001-01). The exact pre-cryopreservation nucleated cell content is provided on the container label and accompanying records.

Store HEMACORD at or below -150 °C until ready for thawing and preparation.

17 PATIENT COUNSELING INFORMATION

Discuss the following with patients receiving HEMACORD:

- Report immediately any signs and symptoms of acute infusion reactions, such as fever, chills, fatigue, breathing problems, dizziness, nausea, vomiting, headache, or muscle aches.
- Report immediately any signs or symptoms suggestive of graft-vs.-host disease, including rash, diarrhea, or yellowing of the eyes.

INSTRUCTIONS FOR PREPARATION FOR INFUSION

1 REQUIRED EQUIPMENT, REAGENTS, AND SUPPLIES

Equipment Biological Safety Cabinet (BSC)
Refrigerated blood bank centrifuge
Plasma extractor
Digital balance
Tube sealer compatible with PVC plastic
Automated cell counter
Microscope and chamber for determining cell count and viability (optional)
Water bath (4 liters or more)
Canister opening tool
Orbital Rotator

Reagents
5% Albumin (human), USP
10% Dextran 40, USP
Bacterial culture bottles (aerobic and anaerobic)

Supplies
Cell Wash/Infusion Bag Set (Transplant Set) (included with HEMACORD)
Sterile Disposable Syringes: 3 mL, 30 mL and 60 mL
Sterile tubing
18 gauge injection needles
Sterile gloves
Hemostats
Sterile small plastic zipper-lock bags
Alcohol prep pads
Iodine swab sticks
Sampling site couplers
Tubes for cell counts, progenitor assays (optional)
Protective cryogloves
Transfer pack containers 300 mL
Instructions for preparation for infusion

2 VERIFICATION OF PRODUCT IDENTITY

HEMACORD is shipped frozen in a steel canister that is contained in an insulating foam sleeve. HEMACORD must be kept at or below -150 °C, either inside the container used for shipping (Dry-Shipper) or in a Liquid Nitrogen (LN2)-cooled storage device at the Transplant Center (recommended).

The bar-coded ID label of the product is affixed to the canister (Figure 1).

Figure 1

1. Check the HEMACORD ID label to confirm its identity with the ID of the expected product as soon as it is received.
2. Wearing protective cryogloves, transfer the HEMACORD from the Dry-Shipper to the vapor phase of a LN2 storage tank.
3. Use the canister opening tool to pry canister open at top and bottom, as shown below in Figures 2 and 3.
  Figure 2.
  Figure 3.
4. Work carefully to avoid damaging the frozen plastic product bag.
5. Check the bar-coded label on the product against your records to verify that the bar-coded and visually-readable printed number absolutely conforms to the information previously provided and the documentation included with the HEMACORD product.
6. Document this check on the “Unit Receipt Form” document received with the product.

NOTE: | If there is any error or ambiguity with regard to the product ID, close the canister and keep the product at LN2 temperature. Immediately advise the staff of the New York Blood Center, Inc. (NYBC) and the transplant physician . Do not proceed until the problem is resolved. If your LN2 storage tanks have no space to store the product in its canister and insulated sleeve, add LN2 to the NYBC dry-shipper to maintain the product frozen until a completely satisfactory determination is made.

3 METHOD

3.1 Preparation of Thawing Solutions

1. Prepare the thawing solution (also called reconstitution solution) at room temperature, mixing equal volumes of 10% Dextran 40 and 5% human albumin, in a biological safety cabinet. The final concentration in the thawing solution is 5% Dextran 40 and 2.5% human albumin.
2. Attach an 18 gauge needle to a 30 cc syringe. Draw approx. 12.5 mL of 10% Dextran 40 and approx. 12.5 mL of 5% human albumin into the syringe. The contents of this syringe are to be used for diluting the cell suspension after thawing.
3. Fit 18 gauge needles to three 60 mL syringes. Draw 30 mL of 10% Dextran 40 and 30 mL of 5% human albumin into each syringe. Two of these 60 mL syringes will be used in steps “l” and “o” in section 3.4 of this procedure. The third syringe will be used in step “l” of section 3.5.
4. Alternatively, prepare the thawing solution in a 300-mL transfer bag by adding, using syringes, 150 mL 10% Dextran 40 and 150 mL 5% albumin.

3.2 Thawing HEMACORD

Wearing protective cryogloves, remove the canister with HEMACORD from the LN2 container. Keep the canister in the vapor phase, just above the surface of the LN2 for 5-10 minutes before proceeding.

Note: If two different HEMACORD products are stored in the LN2 container at the same time, open one canister at a time with the canister opening tool as described above. Carefully check the ID number on the labels attached to the canister and the product, respectively. Close the canister and leave it in the vapor phase for 5-10 min. before proceeding.

1. Open canister with the canister opening tool as described above.
2. Work carefully to avoid damaging the frozen plastic product bag. Remember that plastic at this temperature is very brittle and breaks easily.
3. Examine the bag for breaks or cracks and document this inspection on the appropriate form.
4. Remove the HEMACORD from the canister.
  Caution! Do not handle the plastic bags at liquid nitrogen temperature with the tongs intended for metal canisters, as this may rip the bag. Do not allow the product or tubing to bend as it may crack. Do not press on, bend or stretch the frozen bridges of the bag or segment seal: they are brittle and might break. (Figures 4a. and 4b.)
  Figure 4a. HEMACORD in two-compartment freezing bag after removal from LN2 storage and opening the canister (front view). Arrows point to sealed bridges disclosing folding of the bridges.
  Figure 4b. Same bag as in Figure 4a. (back view).
5. Put the HEMACORD inside a zipper-locked plastic bag, let the air out and close the bag. Place the bag with the HEMACORD in a warm water bath at approximately 38°C.
6. To accelerate and homogenize thawing, carefully agitate the product bag in the water and gently knead its contents.
7. Inspect and watch for leakage. If product leaks out into the zipper-locked bag, find the site of the leak in the freezing bag and position the bag so as to prevent further escape of product. While maintaining the bag in that position, finish thawing the product. (See Section 5 for emergency product recovery in the event of a container failure.)
8. As soon as the bag’s contents become slushy, remove the bag from the water bath and place it inside a biological safety cabinet.

3.3 Connecting the Freezing Bag to the Transplant Set

The procedure to restore the osmolarity of the HEMACORD cell suspension, and either remove the supernatant with DMSO or simply dilute the thawed HEMACORD, is assisted by a sterile, empty, transplant bag set designed with two spike tubes to drain both compartments of the freezing bag (see Figure 5: “Cell Wash/Infusion Bag Set”). The Cell Wash/Infusion Bag Set is included with this shipment.

Note: The following procedure must be done in a biological safety cabinet.

Figure 5. Cell Wash/Infusion Bag Set

1. Close all clamps on the Cell Wash/Infusion Bag Set.
2. Remove the HEMACORD freezing bag from the zipper-locked bag.
3. Disinfect the covers of both ports of the freezing bag with iodine.
4. Using a clean and disinfected scissors, cut off the hermetically sealed covers of the freezing bag’s spike ports (Figure 6).
  Figure 6.
5. Disinfect the cut surfaces of the spike port area of the freezing bag using iodine swab sticks (Figure 7).
  Figure 7.
6. Insert the spikes of the Cell Wash/Infusion Bag Set into the ports of the freezing bag.
7. Label the transplant bag (shown in Figure 5) with HEMACORD ID number and the name of the recipient (or label according to local standard operating procedure).

3.4 Reconstitute (dilute) the thawed HEMACORD

The amount of thawing solution used for HEMACORD is at least 5 times the volume of the frozen product including the cryoprotectant. For example, 25 mL products are diluted to 170 mL total, and thus, a volume of 145 mL of thawing solution is required to make the final volume of 170 mL in a transplant bag.

1. Add first a volume of thawing solution equal to the volume of thawed HEMACORD (1:1 ratio).
2. Attach the 30 cc syringe with the 25 mL thawing solution to the female luer lock of the Cell Wash/Infusion Bag Set.
3. Open PC-1, PC-2 and PC-3 (see Figure 5 above) and slowly introduce half (~12.5 mL) of the thawing solution to the 25 mL product in the freezing bag while mixing the fluids in the bag using an orbital rotator.
4. Rinse well to remove cells from the bag’s ports.
5. Close PC-3. Open PC-4 and drain the contents from the freezing bag into the transplant bag.
6. Close PC-1 and PC-2. Open PC-3.
7. Slowly add the remaining thawing solution (~12.5 mL) to the transplant bag while mixing the fluids in the bag.
8. Close PC-3.
9. Allow approx. 5 minutes for equilibration.
10. Open PC-1 and PC-2. Pass the diluted HEMACORD back and forth between the transplant bag and the freezing bag in order to more completely wash all cells out of the freezing bag and into the transplant bag.
11. Close PC-1 and PC-2.
12. Attach a syringe with 60 mL thawing solution to the luer lock.
13. Open PC-3.
14. Transfer the 60 mL solution to the diluted HEMACORD in the transplant bag while mixing the fluids in the bag.
15. Repeat with a second 60 mL syringe. The final volume should be approx. 170 mL (50 mL diluted HEMACORD with 120 mL thawing solution).
16. Close PC-3. Open PC-1 and PC-2.
17. Pass the reconstituted HEMACORD back and forth between the transplant bag and the freezing bag in order to wash all cells completely out of the freezing bag and into the transplant bag.
18. Close PC-4.
19. Seal the Cell Wash/Infusion Bag Set tubing between PC-4 and IP-1.
20. Cut through seal to separate the transplant bag from the freezing bag.
21. Discard the freezing bag, the luer lock, and the connecting tubing.
22. The reconstituted product can be used for infusion into a patient with or without the additional step of DMSO removal (Section 3.5 below).
23. The recommended expiration time of the reconstituted unwashed HEMACORD is four hours either at room temperature or at 4 °C from the time of thaw.
24. Remove a small volume from the reconstituted product for Complete Blood Counts (CBC), CFU, CD34+ counts, viability, and sterility samples (bacterial and fungal cultures) as per transplant center procedures.
  NOTE: If more than four hours elapse between thawing and infusion, an aliquot of the product should be removed and tested immediately before administration to the patient to determine the cell viability of the infused product.
25. Call the Transplant Unit to advise them that the product is ready for infusion if you do not intend to remove the cryoprotectant.

3.5 Removing the Cryoprotectant (Washing)

1. Place the transplant bag and the transfer bag in a centrifuge cup.
2. Fully support the transplant bag with inserts to prevent formation of creases during centrifugation (as shown in Figure 8 below).
  Figure 8.
3. Close SC-1 securely.
4. Centrifuge at 400 x G for 20 minutes at 10°C.
5. After centrifugation, carefully remove the bags from the centrifuge bucket without disturbing the cellular pellet in the transplant bag.
6. Place the transplant bag in the plasma extractor.
7. Using SC-1 to adjust the flow, very slowly transfer approximately 2/3 of the supernatant (Supernatant-1) to the transfer bag avoiding the passage of cells.
8. Leave approximately 1/3 of supernatant with the cells (white and sedimented red cells in the diagram above). If you detect passage of cells to the transfer bag, return the contents to the transplant bag, resuspend the cells, and repeat the centrifugation or centrifuge only the Supernatant-1 bag (as described below).
9. Empty the tubing between the bags by pushing air from the transfer bag to the transplant bag.
10. Close SC-1.
11. Seal the tubing between the bags close to the transplant bag. Cut through the seal and disconnect the transfer bag with the Supernatant-1 from the transplant bag with the cellular pellet (product).
12. Resuspend the cellular pellet by slowly adding (with a syringe) 25-50 mL of the thawing solution through the IP-1, with continuous mixing. The resuspended cells constitute the Sediment-1 (the graft).
13. The weight of the empty transplant bag is 23.6 g if cut and sealed as shown below (Figure 9). Calculate the weight of the Sediment-1 by weighing the filled transplant bag and subtracting 23.6 g.
14. Remove a small volume from the Sediment-1 for cell count, viability determination, and sterility (bacterial and fungal cultures).
15. The recommended expiration time for HEMACORD after the removal of the cryoprotectant is 24 hours from the date and time of thaw. Store the product at 4 °C in a blood storage refrigerator until the product is used.
  Figure 9.
16. Inspect the supernatant for escaped cells, even if there is no appearance of escape.
17. Express 10 mL from the Supernatant-1 bag into a conical centrifuge tube (accurate volume will help the accuracy of estimations).
18. Centrifuge at 600 x G for 10 minutes.
19. Carefully aspirate 9.5 mL of supernatant without disturbing the (possible) cell pellet in the tip of the tube.
20. Resuspend the cell pellet thoroughly in the 0.5 mL of supernatant and load into a cell-counting chamber.
21. Count the nucleated cells per microliter and calculate the total number of cells in the remaining volume of Supernatant-1.
22. Determine the number of nucleated cells in Supernatant-1 per kg of patient’s weight. The transplant physician may decide whether to add these cells to Sediment-1 cells (the graft) in cases where the Sediment-1 cell dose is low or borderline.
23. If collection of escaped cells from the bag containing Supernatant-1 is desired:
  1. Centrifuge the Supernatant-1 bag at 400 X G for 20 minutes at 10 °C to sediment the cells.
  2. In a laminar flow hood, connect a 300 mL transfer bag to the bag containing the centrifuged product.
  3. Position the bag in the plasma extractor and express the new supernatant (Supernatant-2) into the transfer bag, leaving the sedimented cells (Sediment-2) in the original bag.
  4. Seal the tubing between the bags, cut through the seal, and disconnect the transfer bag with the Supernatant-2 from the original bag with the Sediment-2.
  5. Resuspend the Sediment-2 in 10-15 mL thawing solution, using a syringe and mixing gently. The transplant physician may modify the volume for injection if preferred. If volume modification is desired, resuspend the cellular pellet to the final volume by injecting with thawing solution.
  6. Weigh the Supernatant-2 bag and the Sediment-2 bag, and calculate the volumes by subtracting the weight of the empty bags similarly sealed.
  7. Remove a small volume from the Sediment-2 for cell count, viability determination, and sterility testing.
24. Bring the transplant bag (Sediment-1 bag) to the Transplant Unit, even if the second bag (Sediment-2 bag) is being prepared; the second bag can be infused separately afterwards.

4. ADMINISTRATIVE REQUIREMENTS

1. Prepare a report on the procedure. Note the condition of the HEMACORD bag, including whether and at what stage leaks or cracks were detected. Record the following:
  HEMACORD ID number
  Date of receipt of the HEMACORD
  Liquid Nitrogen Storage conditions in your facility
  Date of thawing
  Volume of the final product
  Total nucleated cell (TNC) count, CD34+ content
  Viability of the cells recovered (TNC or CD34+ cells) and the method used
  Results of bacterial and fungal cultures
2. E-mail or fax a copy of the report to the New York Blood Center, Inc.
  Email: ncbp@nybloodcenter.org
  Fax: (718) 707-3747
3. Keep a copy for your processing lab records.
4. Return the dry shipper to the New York Blood Center, Inc. The return address is:
  New York Blood Center, Inc.
  National Cord Blood Program
  45-01 Vernon Blvd.
  Long Island City, NY 11101
  Ph: (718) 706-5211
  Fax: (718) 707-3741

5. EMERGENCY PRODUCT RECOVERY IN THE EVENT OF A CONTAINER FAILURE

1. To prevent accidental fracture, handle the HEMACORD bags with extreme caution when removing them from the protective metal cassettes, during inspection, and during the thawing process.
2. Perform the thawing process in a controlled laboratory environment that provides appropriate equipment and supplies for post-thaw sampling and/or bag rescue, as well as dedicated space and personnel for product preparation.
3. To mitigate the extreme temperature change from storage at -196 °C (Liquid Nitrogen phase) to thawing at 38°C, and possible sudden vaporization of liquid nitrogen in recess of the bag or tubing, hold the HEMACORD bag in the vapor phase for a few minutes following removal from the liquid phase of nitrogen before removal for thawing.
4. To prevent an accidental drop onto the floor, handle HEMACORD bags over a flat surface, such as a table.
5. Place HEMACORD bags in individual sterile zipper-locked bags prior to thawing to facilitate salvage of the product and to reduce contamination in case of an unanticipated problem.
6. If the HEMACORD bag is obviously fractured upon removal from cold storage, or if it fractures during the thawing process, please notify the Processing Laboratory of the National Cord Blood Program at the New York Blood Center [phone number: 718-706-5211 or 1-866-767-NCBP (1-866-767-6227)] as soon as possible. Notify the transplant physician and the laboratory director immediately.
7. It is the transplant physician’s (or designee’s) responsibility to determine whether the HEMACORD product will be used or discarded and whether additional product(s) are to be requested for infusion.
8. If the transplant physician (or designee) determines that the product in a ruptured bag should be used, the HEMACORD product may be recovered as follows:
  1. Place the ruptured bag into the sterile zipper-locked plastic bag to prevent further loss and/or contamination of the product during the thawing process.
  2. Thaw the product according to the Section 3 above. Small leaks or tears of the ruptured bag can be blocked off with hemostat clips.
  3. Withdraw the thawed product from the freezing bag and any product from the zipper-locked bag into one or more 60 mL syringe(s) with sterile tubing attached.
  4. Inside a biological safety cabinet, transfer the product into a new bag using a sterile syringe. (This new bag could be either the sterile transplant bag that is provided with the HEMACORD product or a bag of a stocked salvage kit that should be readily available in the thawing laboratory for use in these situations.)
  5. Save an aliquot of the product to send for gram stain and bacterial and fungal cultures.
  6. Dilute (reconstitute) the thawed HEMACORD and remove the cryoprotectant according to the procedure described above or administer the diluted product to the patient as per transplant physician’s instructions.
  7. It is the transplant physician’s (or designee’s) responsibility to determine whether to treat the patient with broad-spectrum antibiotic coverage and the necessity for an infectious disease consultation.
  8. If possible, place the ruptured bag (with or without the product) into a biohazard bag and save for reference when notifying the National Cord Blood Program at the New York Blood Center. This staff will notify the manufacturer and provide information for returning the bag to the manufacturer for evaluation.
  9. Notify the National Cord Blood Program at the New York Blood Center [phone number: 718-706-5211 or 1-866-767-NCBP (1-866-767-6227)].

Distributed by:
New York Blood Center, Inc.
45-01 Vernon Boulevard
Long Island City, NY 11101
License No. 0465
Issued: 02/2012

Package Label - Principal Display Panel - 25 mL Bag

Package Label - Principal Display Panel - 25 mL Canister

PACKAGE LABEL

Package Label - Principal Display Panel - NDC 76489-001-01